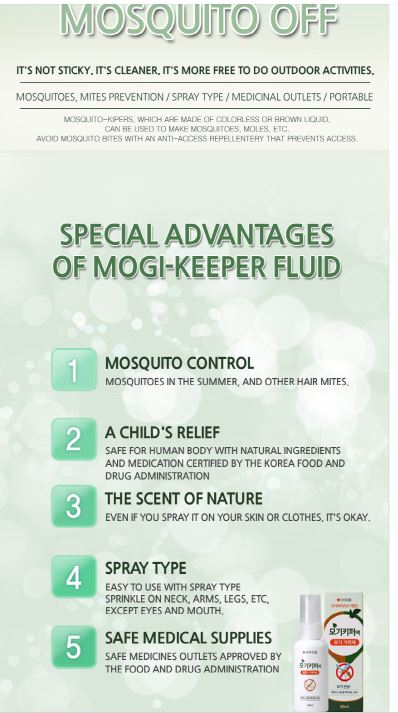 DRUG LABEL: MOSQUITO BUG OFF
NDC: 72988-0005 | Form: LIQUID
Manufacturer: Lydia Co., Ltd.
Category: otc | Type: HUMAN OTC DRUG LABEL
Date: 20210628

ACTIVE INGREDIENTS: DIETHYLTOLUAMIDE 10 g/100 mL
INACTIVE INGREDIENTS: WATER; DIPROPYLENE GLYCOL

Drug Facts

ACTIVE INGREDIENT

DIETHYLTOLUAMIDE

INACTIVE INGREDIENT

ET5HANOL, PURIFIED WATER, DIPROPYLENE GLYCOL, FRAGRANCE

PURPOSE

mosquito repellents that prevent access to mosquitoes.

keep out of reach of the children

INDICATIONS AND USAGE

You can spray it on your skin or clothes.

do not use for the following people: infants under six months

do not use excessive amounts or for long periods of time beyond the required

do not use it in an enclosed area

DOSAGE AND ADMINISTRATION

for external use only